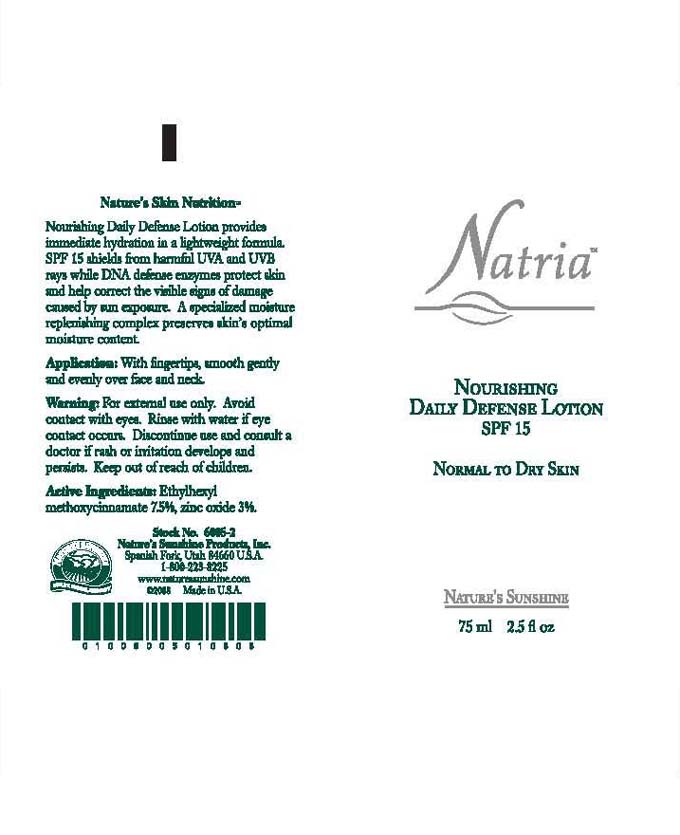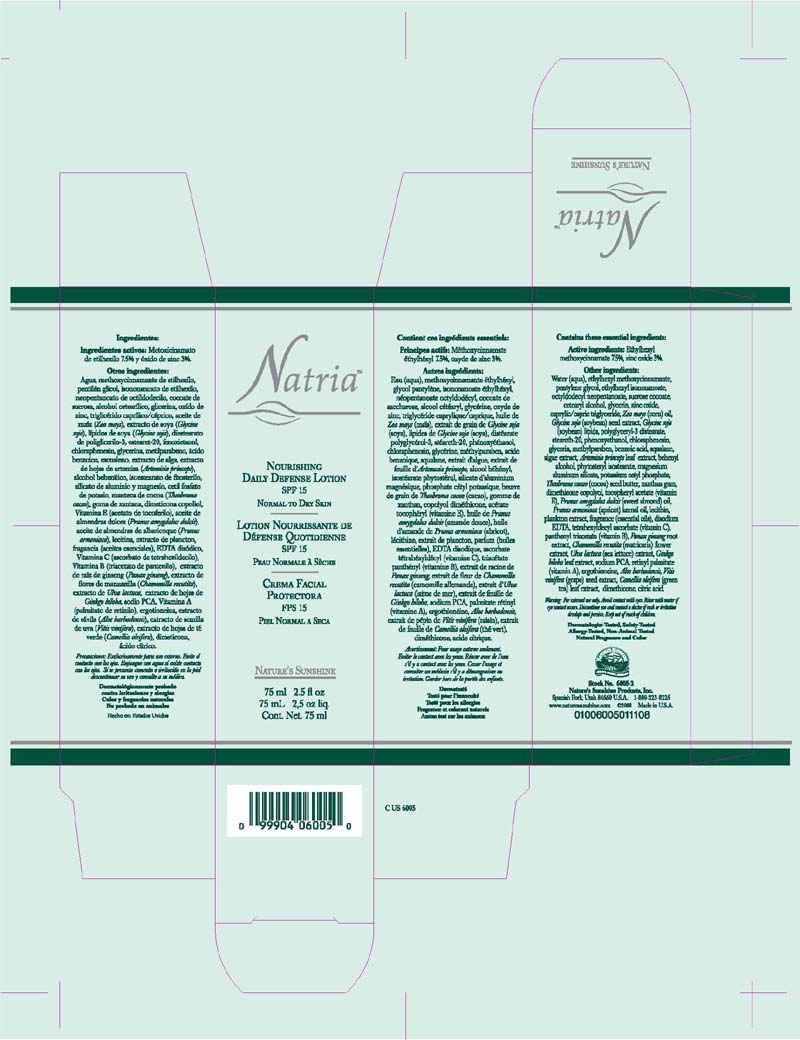 DRUG LABEL: Natria
NDC: 44717-533 | Form: CREAM
Manufacturer: Wasatch Product Development
Category: otc | Type: HUMAN OTC DRUG LABEL
Date: 20100701

ACTIVE INGREDIENTS: OCTINOXATE 7.5 mL/100 mL; ZINC OXIDE 2.5 mL/100 mL

Nourishing Daily Defense Lotion SPF15

Active Ingredients

Octinoxate 7.5%

Zinc Oxide 3%

WARNINGS

Warnings: For external use only. Avoid contact with eyes. Rinse with water if eye contact occurs. Discontinue use and consult a doctor if rash or irritation develops and persists. Keep out of reach of children.

INDICATIONS AND USAGE

Application: with fingertips, smooth gently and evenly over face and neck

INACTIVE INGREDIENT

Inactive Ingredients: Water (Aqua), Ethylhexyl Methoxycinnamate, Pentylene Glycol, Ethylhexyl Isononanoate, Octyldodecyl Neopentanoate, Sucrose Cocoate, Cetearyl Alcohol, Glycerin, Zinc Oxide, Caprylic/Capric Triglyceride, Zea mays (corn) oil, glycine soja (soybean) seed extract, glycine soja (soybean) lipids, polyglyceryl-3 distearate, steareth-20, phenoxyethanol, chloraphenesin, glycerin, methylparaben, benzoic acid, squalane, algae extracts, artemisia princeps leaf extract, behenyl alcohol, phytosteryl isostearate, magnesium aluminum silicate, potassium cetyl phosphate, Theobroma cacao (Cocoa) seed butter, xanthan gum, dimethicone copolyol, tocopheryl acetate (vitamin E), prunus amygdalus (sweet almond) oil, prunus armensca (apricot) kernel oil, lecithin, plankton extract, fragrance (essential oils), disodium EDTA, tetrahexyldecyl ascorbate (vitamin C), panthenyl triacetate (vitamin B), panax ginseng root extract, chamomilla recutita (marticaria) flower extract, ulva lactuca (sea lettucs) extract, ginkgo biloba leaf extract, sodium PCA, retinyl palmitate (vitamin A), ergothioneine, aloe barbadensis, vitis vinifera (grape) seed extract, camellia oleifera (green tea) leaf extract, dimethicone, citric acid.

PACKAGE LABEL

Natria

Nourishing Daily Defense Lotion SPF 15

75 ml/ 2.5 fl.oz.